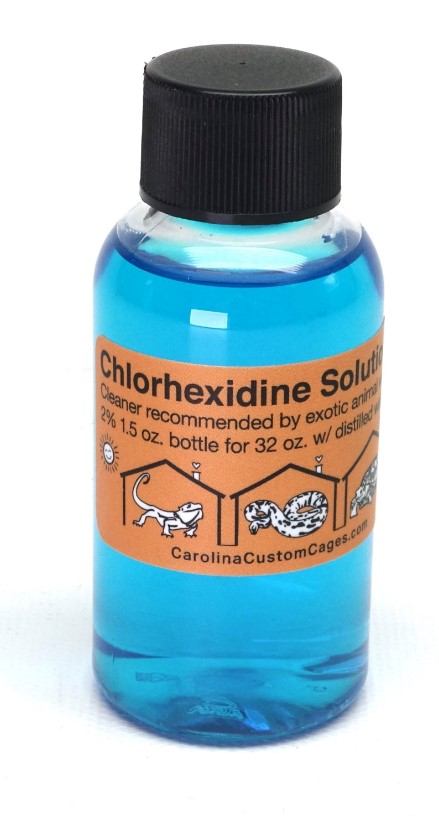 DRUG LABEL: Carolina Custom Cages Chlorhexidine
NDC: 86182-001 | Form: SOLUTION
Manufacturer: Carolina Designer Dragons, Inc.
Category: animal | Type: OTC ANIMAL DRUG LABEL
Date: 20230512

ACTIVE INGREDIENTS: CHLORHEXIDINE GLUCONATE 99 g/1 L

Chlorhexidine Solution

Indications

Cleaner recommended by animal vets

Dilution

2% 1.5 oz. bottle for 32 oz. with distilled water

PACKAGE LABEL

Carolina Custom Cages Chlorhexidine